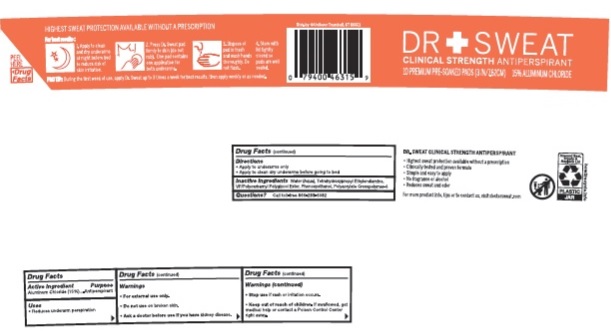 DRUG LABEL: Dr Sweat
NDC: 64942-1633 | Form: LIQUID
Manufacturer: Conopco Inc. d/b/a/ Unilever
Category: otc | Type: HUMAN OTC DRUG LABEL
Date: 20221207

ACTIVE INGREDIENTS: ALUMINUM CHLORIDE 15 g/100 g
INACTIVE INGREDIENTS: WATER; EDETOL; PHENOXYETHANOL; AMMONIUM ACRYLOYLDIMETHYLTAURATE, DIMETHYLACRYLAMIDE, LAURYL METHACRYLATE AND LAURETH-4 METHACRYLATE COPOLYMER, TRIMETHYLOLPROPANE TRIACRYLATE CROSSLINKED (45000 MPA.S)

Dr Sweat Clinical Strength Antiperspirant

DR SWEAT CLINICAL STRENGTH ANTIPERSPIRANT - aluminum chloride liquid

Dr Sweat Clinical Strength Antiperspirant

Drug Facts

Active ingredient

Aluminum Chloride (15.0%)

Purpose

Antiperspirant

Uses

• reduces underarm perspiration

Warnings

• For externaluse only.
• Do not use on broken skin .
• Ask a doctor before use if you have kidney disease.
• Stop use if rash or irritation occurs.

• Keep out of reach of children.

If swallowed, get medical help or contact a Poison Control Center right away.

Directions

• Apply to underarms only
• Apply to clean dry underarms before going to bed.

Inactive ingredients

Water (Aqua), Tetrahydroxypropyl Ethylenediamine, VP/Polycarbamyl Polyglycol Ester, Phenoxyethanol, Polyacrylate Crosspolymer-6

Questions?

Call toll-free 866-269-6082

OTHER SAFETY INFORMATION

• Highest sweat profession available without a prescription
• Clinically tested and proven formula
• Simply and easy to apply
• No fragrance or alcohol
• Reduces sweat and odor